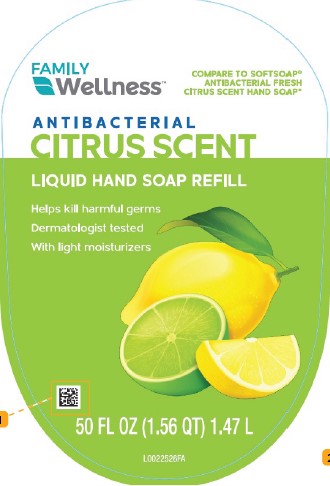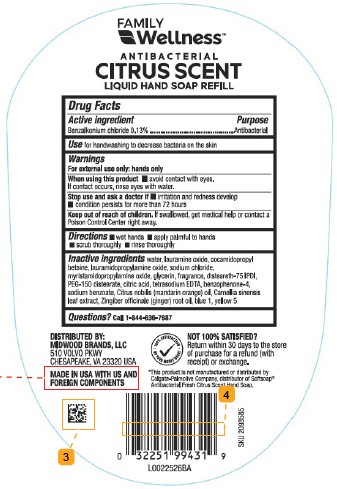 DRUG LABEL: Benzalkonium Chloride
NDC: 55319-633 | Form: LIQUID
Manufacturer: Family Dollar Stores, Inc
Category: otc | Type: HUMAN OTC DRUG LABEL
Date: 20260224

ACTIVE INGREDIENTS: BENZALKONIUM CHLORIDE 1.3 mg/1 mL
INACTIVE INGREDIENTS: TETRASODIUM EDTA; LAURAMINE OXIDE; GREEN TEA LEAF; DISTEARETH-75 IPDI; CITRIC ACID; SODIUM BENZOATE; BENZOPHENONE-4; FD&C BLUE NO. 1; GINGER OIL; FD&C YELLOW NO. 5; SODIUM CHLORIDE; PEG-150 DISTEARATE; CITRUS NOBILIS (MANDARIN ORANGE) OIL; WATER; COCAMIDOPROPYL BETAINE; LAURAMIDOPROPYLAMINE OXIDE; MYRISTAMIDOPROPYLAMINE OXIDE; GLYCERIN

Family Wellness 633.002/633AC-AD
Antibacterial Hand Soap with Moisturizers – Fresh Citrus

Claims

FAMILY Wellness™

ANTIBACTERIAL

CITRUS SCENT

LIQUID HAND SOAP REFILL

Active ingredient

Benzalkonium chloride 0.13%

Purpose

Antibacterial

Use

for handwashing to decrease bacteria on the skin

Warnings

For external use only: hands only

When using this product

- avoid contact with eyes. If contact occurs, rinse eyes with water.

Stop use and ask a doctor if

- irritation and redness develop
- condition persists for more than 72 hours

Keep out of reach of children.

If swallowed, get medical help or contact a Poison Control Center right away.

Directions

- wet hands
- apply palmful to hands
- scrub thoroughly
- rinse thoroughly

Inactive ingredients

water, lauramine oxide, cocamidopropyl betaine, lauramidopropylamine oxide, sodium chloride, myristamidopropylamine oxide, glycerin, fragrance, disteareth-75 IPDI, PEG-150 distearate, citric acid, tetrasodium EDTA, benzophenone-4, sodium benzoate, Citrus nobilis (mandarin orange) oil, Camellia sinensis leaf extract, Zingiber officinale (ginger) root oil, blue 1, yellow 5

Questions?

Call 1-844-636-7687

Adverse Reaction

DISTRIBUTED BY:

MIDWOOD BRANDS, LLC

510 VOLVO PKWY

CHESAPEAKE, VA 23320 USA

MADE IN USA WITH US AND FOREIGN COMPONENTS

100% SATISFACTION OR YOUR MONEY BACK!

NOT 100% SATISFIED?

Return within 30 days to the store of purchase for a refund (with receipt) or exchange.

Disclaimer

*This product is not manufactured or distributed by Colgate-Palmolive Company, distributor of Softsoap® Antibacterial Fresh Citrus Scent Hand Soap.

Principal Display Panel

FAMILY Wellness™

COMPARE TO SOFTSOAP® ANTIBACTERIAL FRESH CITRUS SCENT HAND SOAP*

ANTIBACTERIAL

CITRUS SCENT

LIQUID HAND SOAP REFILL

Helps kill harmful germs

Dermatologist tested

With light moisturizers

50 FL OZ (1.56 QT) 1.47 L